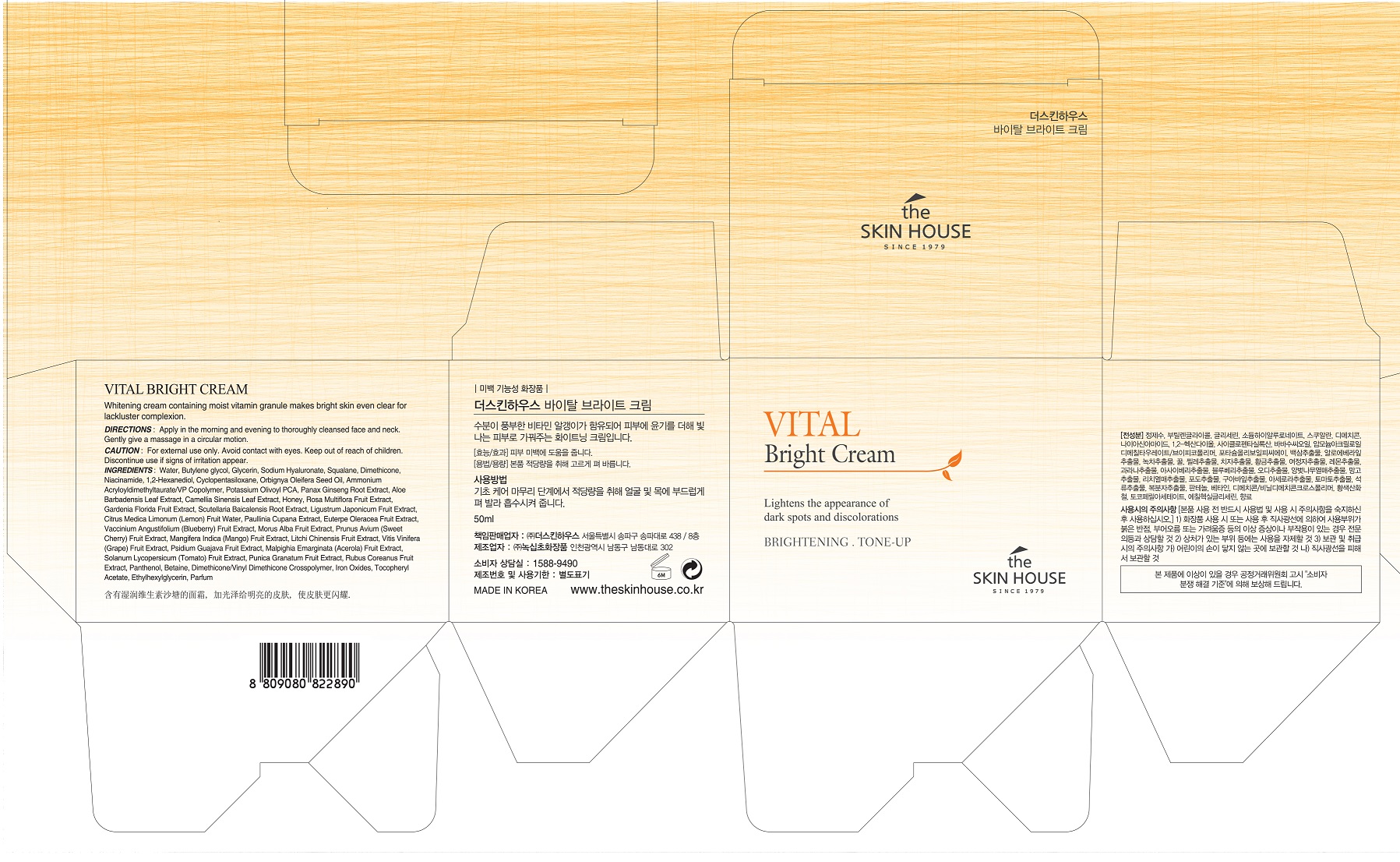 DRUG LABEL: THE SKIN HOUSE Vital BrightCream
NDC: 73590-0025 | Form: CREAM
Manufacturer: NOKSIBCHO cosmetic Co., Ltd.
Category: otc | Type: HUMAN OTC DRUG LABEL
Date: 20200330

ACTIVE INGREDIENTS: NIACINAMIDE 2 g/100 mL
INACTIVE INGREDIENTS: WATER

Drug Facts

ACTIVE INGREDIENT

Niacinamide

INACTIVE INGREDIENT

Water
Glycerin
Sodium Hyaluronate
Butylene glycol
Squalane
Dimethicone
1,2-Hexanediol
Cyclopentasiloxane
Orbignya Oleifera Seed Oil
Ammonium Acryloyldimethyltaurate/VP Copolymer
Potassium Olivoyl PCA
Panax Ginseng Root Extract
Aloe Barbadensis Leaf Extract
Camellia Sinensis Leaf Extract
Honey
Rosa Multiflora Fruit Extract
Gardenia Florida Fruit Extract
Scutellaria Baicalensis Root Extract
Ligustrum Japonicum Fruit Extract
Citrus Medica Limonum (Lemon) Fruit Water
Paullinia Cupana Extract
Euterpe Oleracea Fruit Extract
Vaccinium Angustifolium (Blueberry) Fruit Extract
Morus Alba Fruit Extract
Prunus Avium (Sweet Cherry) Fruit Extract
Mangifera Indica (Mango) Fruit Extract
Litchi Chinensis Fruit Extract
Vitis Vinifera (Grape) Fruit Extract
Psidium Guajava Fruit Extract
Malpighia Emarginata (Acerola) Fruit Extract
Solanum Lycopersicum (Tomato) Fruit Extract
Punica Granatum Fruit Extract
Rubus Coreanus Fruit Extract
Panthenol
Tocopheryl Acetate
Betaine
Dimethicone/Vinyl Dimethicone Crosspolymer
Iron Oxides
Ethylhexylglycerin
Parfum

PURPOSE

skin brightening

keep out of reach of the children

INDICATIONS AND USAGE

apply proper amount to the skin

WARNINGS

For external use only
When using this product

■ if the following symptoms occurs after use, stop use and consult with a skin specialist

red specks, swelling, itching

■ don’t use on the part where there is injury, eczema, or dermatitis

Keep out of reach of children

■ if swallowed, get medical help or contact a person control center immediately